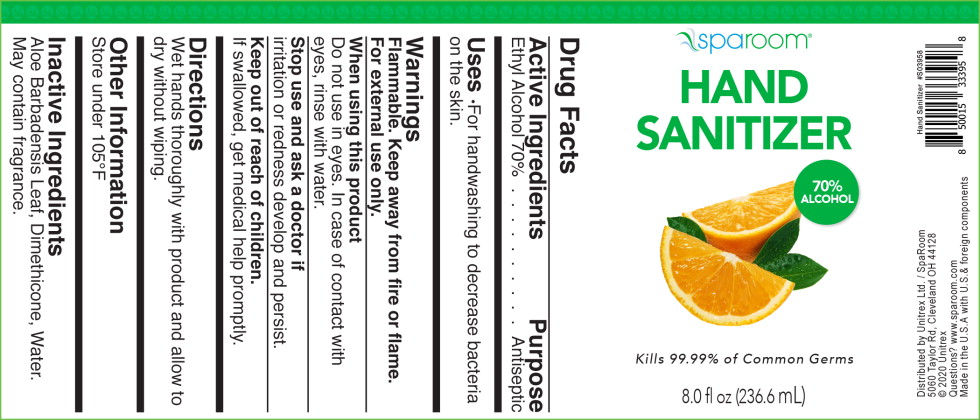 DRUG LABEL: Sparoom Hand Sanitizer
NDC: 66902-645 | Form: LIQUID
Manufacturer: Natural Essentials, Inc.
Category: otc | Type: HUMAN OTC DRUG LABEL
Date: 20250718

ACTIVE INGREDIENTS: ALCOHOL 0.7 mL/1 mL
INACTIVE INGREDIENTS: ALOE VERA LEAF; DIMETHICONE; TRIISOPROPANOLAMINE; WATER

Drug Facts

Active Ingredients

Ethyl Alcohol 70%

Purpose

Antiseptic

Uses

- For handwashing to decrease bacteria on the skin.

Warnings

Flammable. Keep away from fire or flame.

For external use only.

When using this product

Do not use in eyes. In case of contact with eyes, rinse with water.

Stop use and ask a doctor if

irritation or redness develop and persist.

Keep out of reach of children.

If swallowed, get medical help promptly.

Directions

Wet hands thoroughly with product and allow to dry without wiping.

Other Information

Store under 105°F

Inactive Ingredients

Aloe Barbadensis Leaf, Dimethicone, Water.

May contain fragrance.

Principal Display Panel – Bottle Label

sparoom®

HAND
SANITIZER

70%
ALCOHOL

Kills 99.99% of Common Germs

8.0 fl oz (236.6 mL)